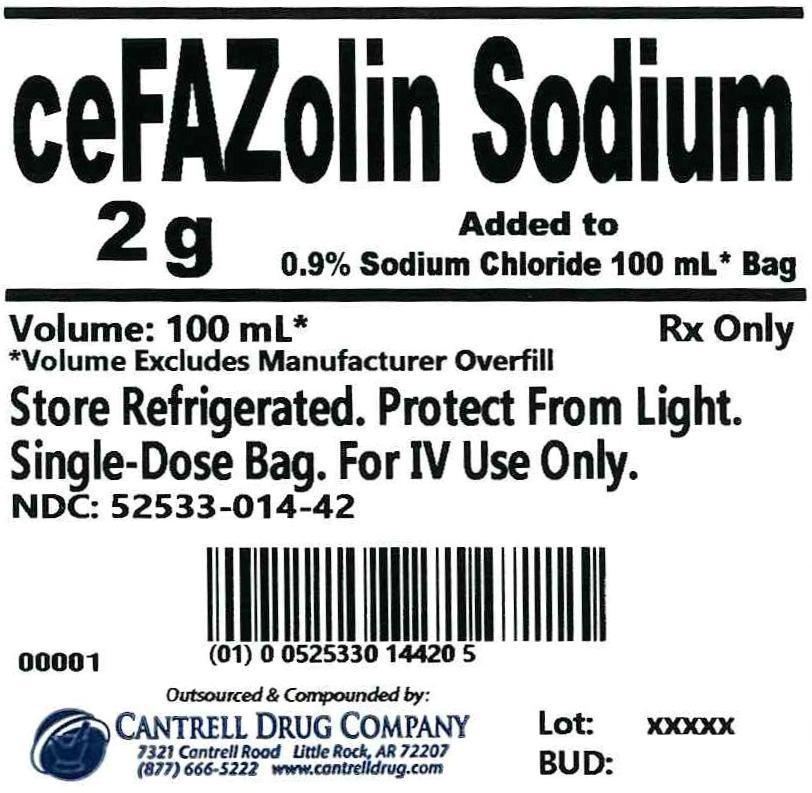 DRUG LABEL: Cefazolin Sodium
NDC: 52533-014 | Form: INJECTION, SOLUTION
Manufacturer: Cantrell Drug Company
Category: prescription | Type: HUMAN PRESCRIPTION DRUG LABEL
Date: 20140409

ACTIVE INGREDIENTS: Cefazolin Sodium 2 g/100 mL
INACTIVE INGREDIENTS: Sodium Chloride 0.9 g/100 mL; Water

Cefazolin Sodium 2 g Added to 0.9% Sodium Chloride 100 mL Bag